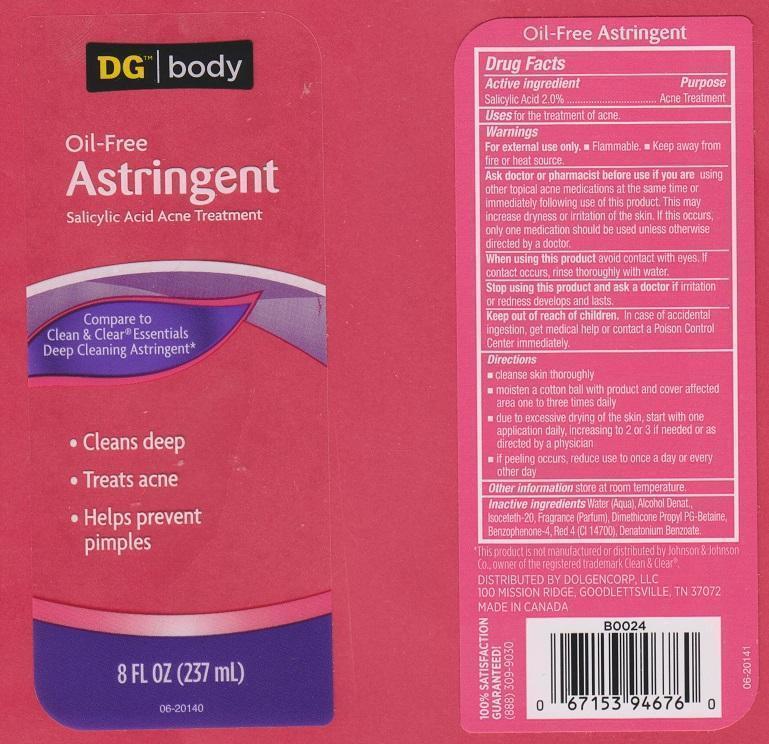 DRUG LABEL: DG BODY
NDC: 55910-101 | Form: LIQUID
Manufacturer: DOLGENCORP INC
Category: otc | Type: HUMAN OTC DRUG LABEL
Date: 20150303

ACTIVE INGREDIENTS: SALICYLIC ACID 20 mg/1 mL
INACTIVE INGREDIENTS: WATER; ALCOHOL; ISOCETETH-20; SULISOBENZONE; FD&C RED NO. 40; DENATONIUM BENZOATE

DRUG FACTS

ACTIVE INGREDIENT

SALICYLIC ACID 2.0%

PURPOSE

ACNE TREATMENT

USES

FOR THE TREATMENT OF ACNE

WARNINGS

FOR EXTERNAL USE ONLY

- FLAMMABLE
- KEEP AWAY FROM FIRE OR HEAT SOURCE

ASK DOCTOR OR PHARMACIST BEFORE USE IF YOU ARE

USING OTHER TOPICAL ACNE MEDICATIONS AT THE SAME TIME OR IMMEDIATELY FOLLOWING USE OF THIS PRODUCT. THIS MAY INCREASE DRYNESS OR IRRITATION OF THE SKIN. iF THIS OCCURS, ONLY ONE MEDICATION SHOULD BE USED UNLESS OTHERWISE DIRECTED BY A DOCTOR

WHEN USING THIS PRODUCT

AVOID CONTACT WITH EYES. IF CONTACT OCCURS, RINSE THOROUGHLY WITH WATER

STOP USING THIS PRODUCT AND ASK A DOCTOR IF

IRRITATION OR REDNESS DEVELOPS AND LASTS

KEEP OUT OF REACH OF CHILDREN

IN CASE OF ACCIDENTAL INGESTION, GET MEDICAL HELP OR CONTACT A POISON CONTROL CENTER IMMEDIATELY

DIRECTIONS

- CLEANSE SKIN THOROUGHLY
- MOISTEN A COTTON BALL WITH PRODUCT AND COVER AFFECTED AREA ONE TO THREE TIMES DAILY
- DUE TO EXCESSIVE DRYING OF THE SKIN, START WITH ONE APPLICATION DAILY, INCREASING TO 2 OR 3 IF NEEDED OR AS DIRECTED BY A PHYSICIAN
- IF PEELING OCCURS, REDUCE USE TO ONCE A DAY OR EVERY OTHER DAY

OTHER INFORMATION

STORE AT ROOM TEMPERATURE

INACTIVE INGREDIENTS

WATER (AQUA), ALCOHOL DENAT., ISOCETETH-20, FRAGRANCE (PARFUM), DIMETHICONE PROPYL PG-BETAINE, BENZOPHENONE-4, RED 4 (CI 14700), DENATONIUM BENZOATE